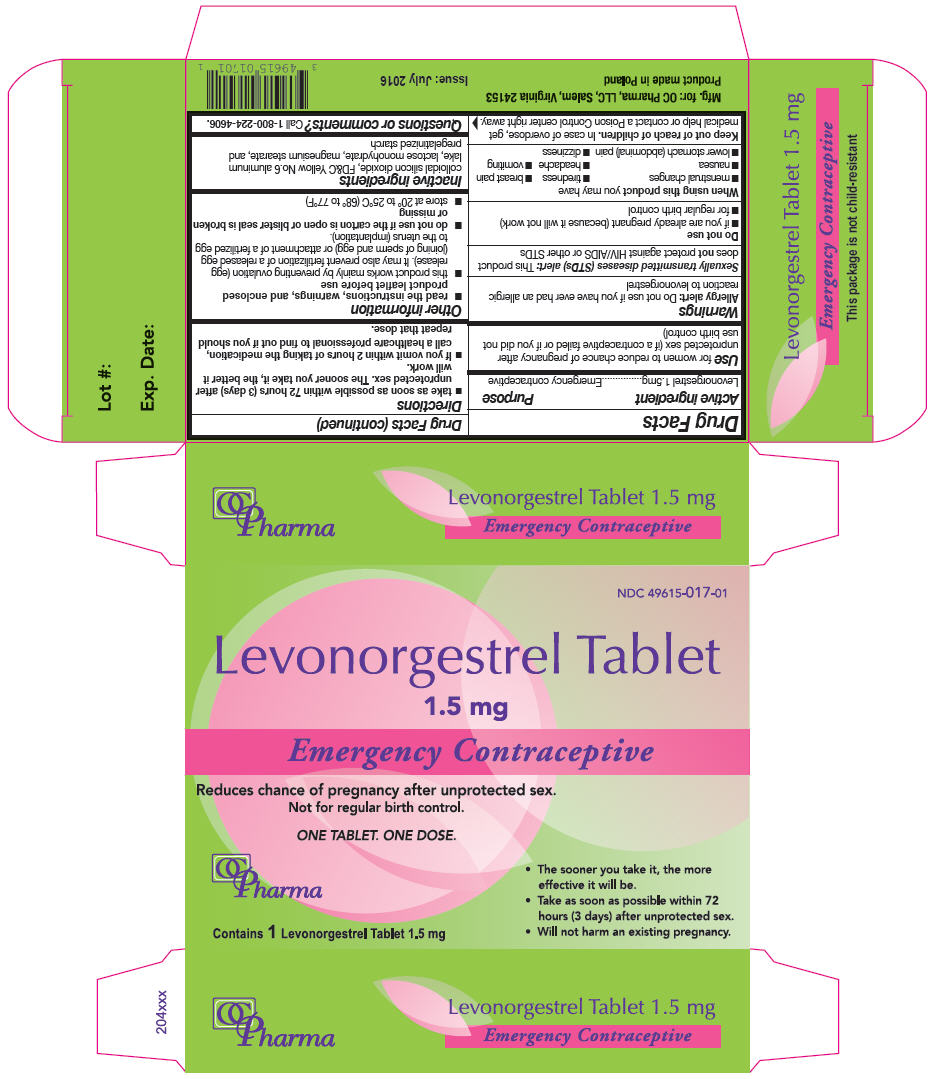 DRUG LABEL: Levonorgestrel
NDC: 49615-017 | Form: TABLET
Manufacturer: OC Pharma, LLC
Category: otc | Type: HUMAN OTC DRUG LABEL
Date: 20171026

ACTIVE INGREDIENTS: Levonorgestrel 1.5 mg/1 1
INACTIVE INGREDIENTS: Silicon Dioxide; FD&C YELLOW NO. 6; Lactose Monohydrate; Magnesium Stearate; Starch, corn

Levonorgestrel Tablets

Drug Facts

Active ingredient

Levonorgestrel 1.5mg

Purpose

Emergency contraceptive

Use

for women to reduce chance of pregnancy after unprotected sex (if a contraceptive failed or if you did not use birth control)

Warnings

Allergy alert

Do not use if you have ever had an allergic reaction to levonorgestrel

Sexually transmitted diseases (STDs) alert

This product does not protect against HIV/AIDS or other STDs

Do not use

- if you are already pregnant (because it will not work)
- for regular birth control

When using this product you may have

- menstrual changes
- tiredness
- breast pain
- nausea
- headache
- vomiting
- lower stomach (abdominal) pain
- dizziness

Keep out of reach of children. In case of overdose, get medical help or contact a Poison Control center right away.

Directions

- take as soon as possible within 72 hours (3 days) after unprotected sex. The sooner you take it, the better it will work.
- If you vomit within 2 hours of taking the medication, call a healthcare professional to find out if you should repeat that dose.

Other information

- read the instructions, warnings, and enclosed product leaflet before use
- this product works mainly by preventing ovulation (egg release). It may also prevent fertilization of a released egg (joining of sperm and egg) or attachment of a fertilized egg to the uterus (implantation).
- do not use if the carton is open or blister seal is broken or missing
- store at 20° to 25°C (68° to 77°F)

Inactive ingredients

colloidal silicon dioxide, FD&C Yellow No.6 aluminum lake, lactose monohydrate, magnesium stearate, and pregelatinized starch

Questions or comments?

Call 1-800-224-4606.

PRINCIPAL DISPLAY PANEL - 1.5 mg Tablet Blister Pack Carton

NDC 49615-017-01

Levonorgestrel Tablet

1.5 mg

Emergency Contraceptive

Reduces chance of pregnancy after unprotected sex.
Not for regular birth control.

ONE TABLET. ONE DOSE.

OC
Pharma

Contains 1 Levonorgestrel Tablet 1.5 mg

- The sooner you take it, the more
  effective it will be.
- Take as soon as possible within 72
  hours (3 days) after unprotected sex.
- Will not harm an existing pregnancy.